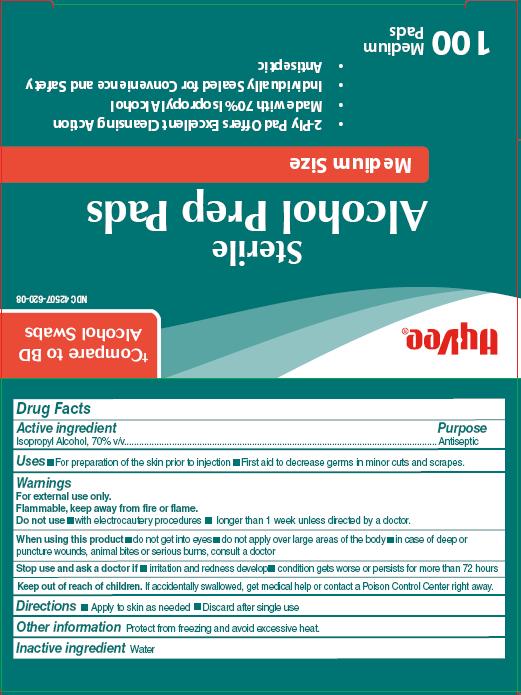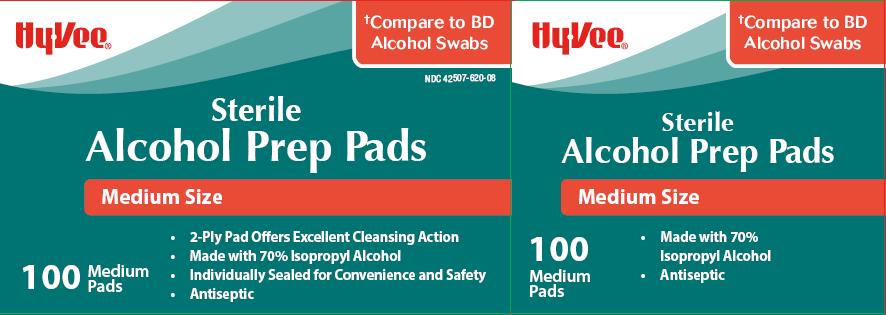 DRUG LABEL: HyVee Alcohol Prep Pads
NDC: 42507-815 | Form: SWAB
Manufacturer: HY-VEE, INC.
Category: otc | Type: HUMAN OTC DRUG LABEL
Date: 20140717

ACTIVE INGREDIENTS: ISOPROPYL ALCOHOL 70 mL/100 mL
INACTIVE INGREDIENTS: WATER

Drug Facts

Active ingredient

Isopropyl alcohol, 70% v/v

Purpose

Antiseptic

Uses

- for preparation of the skin prior to injection
- First aid to decrease germs in minor cuts and scrapes

Warnings

For external use only.

Flammable, keep away from fire or flame.

Do not use

- with electrocautery procedures
- Longer than 1 week unless directed by a doctor
- Do not get into eyes
- Do not apply over large areas of the body
- In case of deep or puncture wounds, animal bites or serious burns, consult a doctor

Stop use and ask a doctor if

- irritation and redness develop
- condition persists for more than 72 hours

Keep out of reach of children.

If swallowed, get medical help or contact a Poison Control Center right away.

Directions

Apply to skin as needed

Discard after single use

Other information

Protect from freezing. Avoid excessive heat.

Inactive ingredients

Water

Package/Label Principal Display Panel

HyVee

Compare to BD Alcohol Swabs

Sterile

Alcohol Prep Pads

Medium Size

2-Ply Pad offers Excellent Cleansing Action

Made with 70% Isopropyl Alcohol

Individually Sealed for Convenience and Safety

Antiseptic

100 Medium Pads